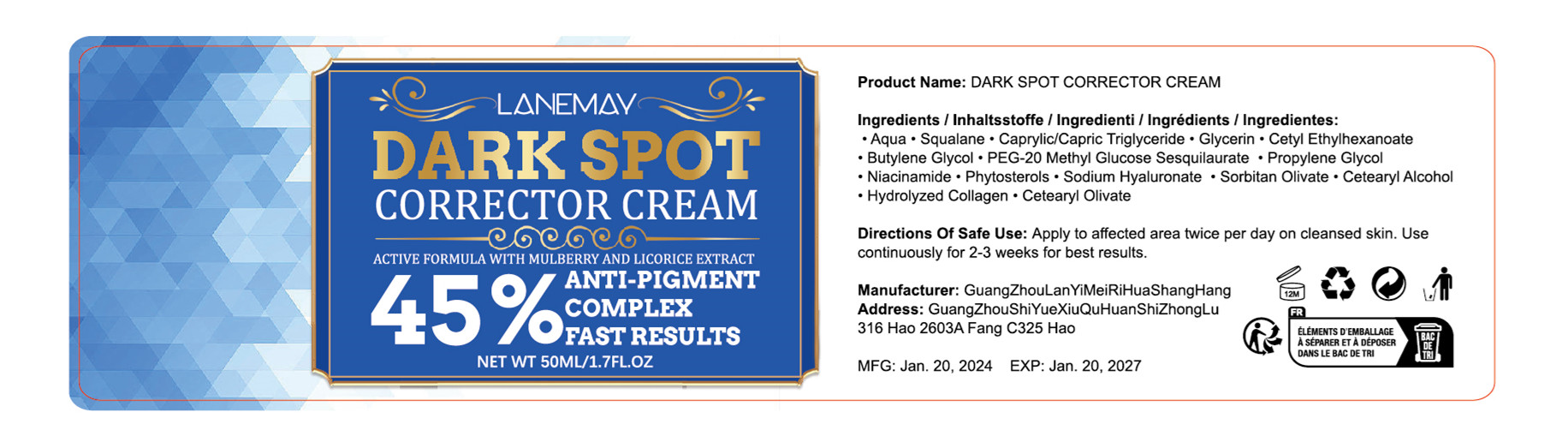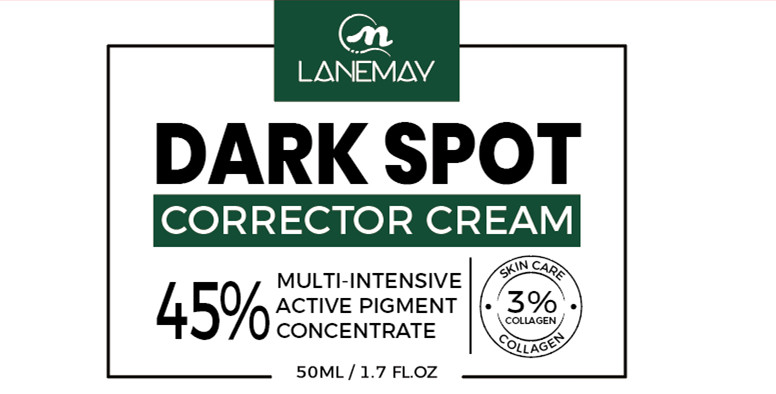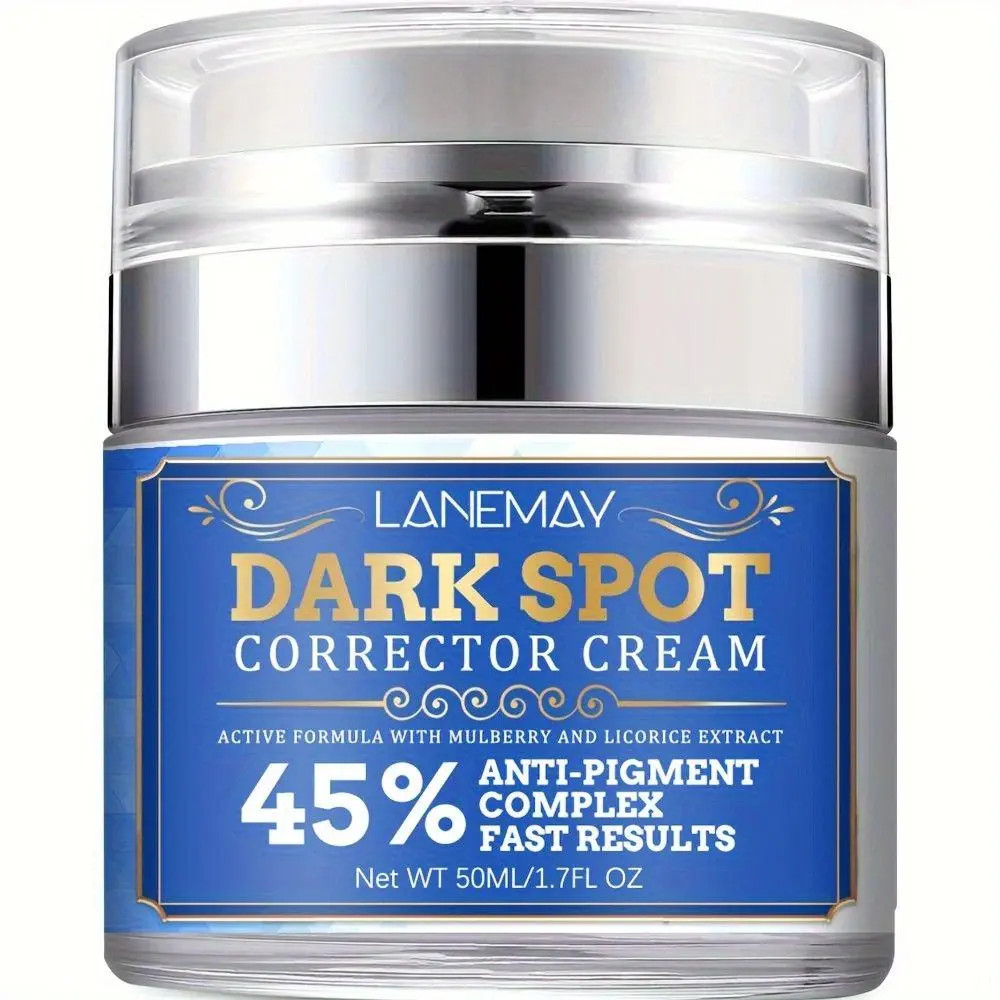 DRUG LABEL: dark spot corrector cream
NDC: 84025-018 | Form: CREAM
Manufacturer: Guangzhou Yanxi Biotechnology Co., Ltd
Category: otc | Type: HUMAN OTC DRUG LABEL
Date: 20240323

ACTIVE INGREDIENTS: CAPRYLIC/CAPRIC/LAURIC TRIGLYCERIDE 5 mg/50 mL; SQUALANE 5 mg/50 mL; GLYCERIN 4 mg/50 mL
INACTIVE INGREDIENTS: WATER

DOSAGE AND ADMINISTRATION

use as a normal facial cream

WARNINGS

Keep out of Children

INACTIVE INGREDIENT

Aqua

INDICATIONS AND USAGE

For daily facial care

Keep out of Children

PURPOSE

dark spot corrector cream

anti-pigment